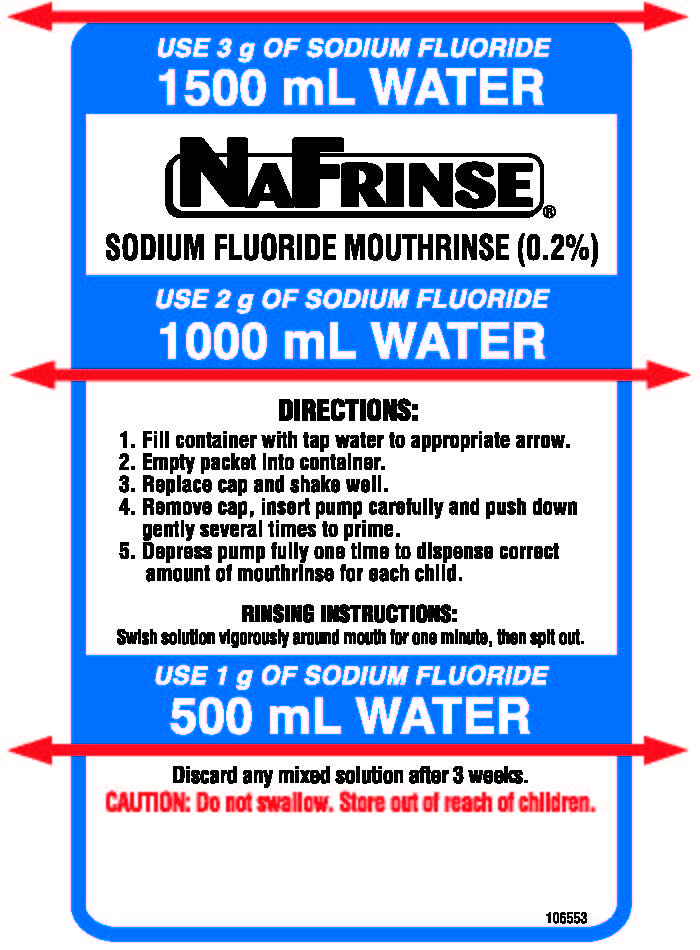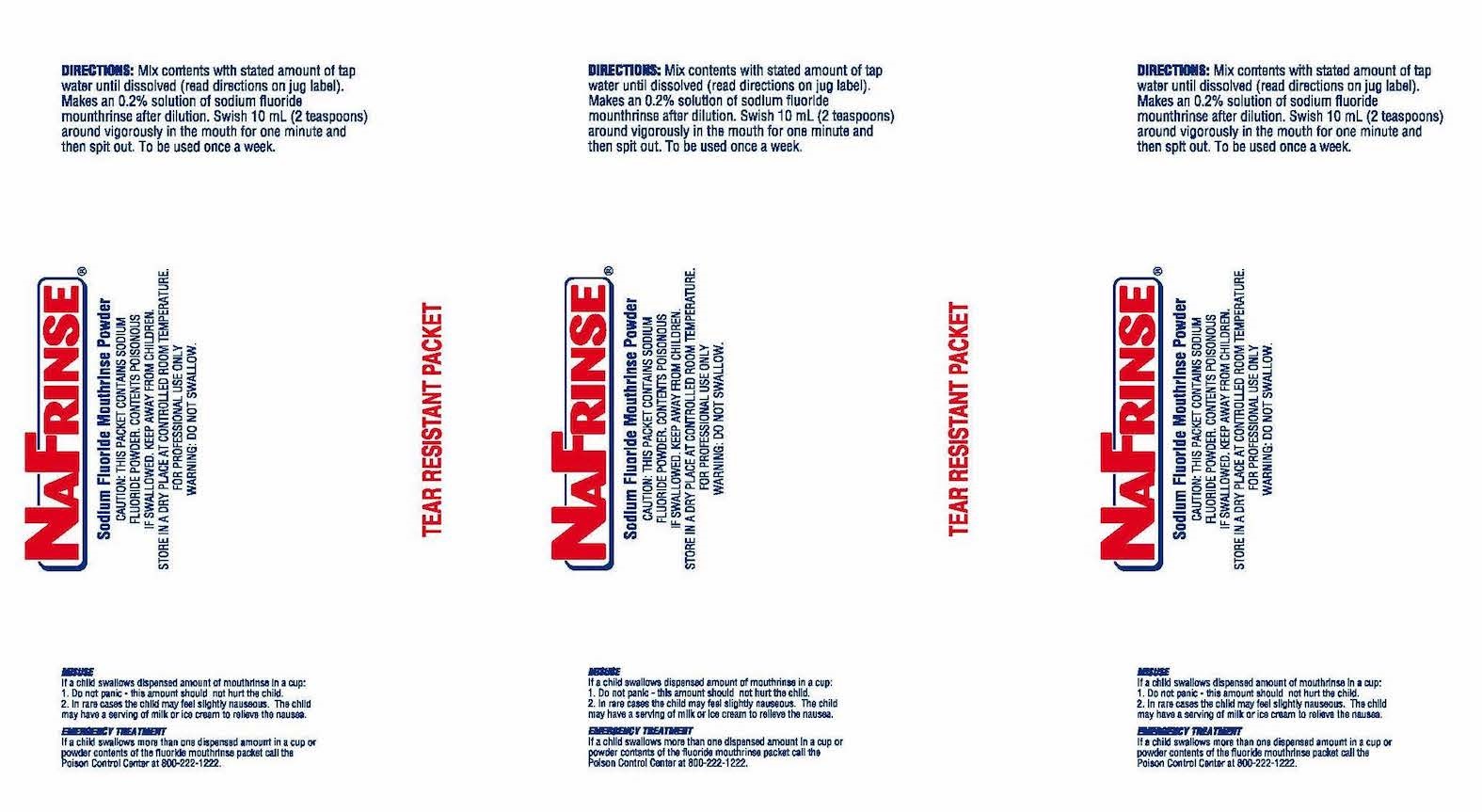 DRUG LABEL: NAFRINSE PACKETSKIT MINT
NDC: 0273-8007 | Form: POWDER
Manufacturer: Young Dental Manufacturing Co 1, LLC.
Category: prescription | Type: HUMAN PRESCRIPTION DRUG LABEL
Date: 20181214

ACTIVE INGREDIENTS: Sodium Fluoride 1 g/1 g
INACTIVE INGREDIENTS: SACCHARIN SODIUM; Potassium Sorbate; ANHYDROUS CITRIC ACID

Convinience KIT -20 pack of Nafrinse packets, a polyethylene jug, dispenser pump, plastic cups, paper napkins, and trash bag with ties

Inactives

Saccharin Sodium, Potassium Sorbate, Citric Acid, Flavoring

Dye

Warning:

This Packet contains sodium fluoride powder, contents poisonous if swallowed. keep away from children. Store in a dry place at controlled room temperature. For professional use only.

DO NOT SWALLOW

MISSUSE If child swallows dispensed amount of mouth rinse in a cup:

1. Do not panic -this amount should not hurt the child

2. In rare cases the child may feel slightly nauseous.

The child may have a serving of milk or ice cream to relieve the nausea. EMERGENCY TREATMENT If a child swallows more than one dispensed amount in a cup or powder contents of the fluoride mouth rinse packet call the Poison Control Center at 800-222-1222

Directions

Mix contents with stated amount of tap water until dissolved (read directions on jug label) Makes an 0.2 % solution of sodium fluoride mouthrinse aftert dilution. Swish 10 ml (2 teaspoons) around vigorously in the mouth for one minute and then spit out. To be used once a week.